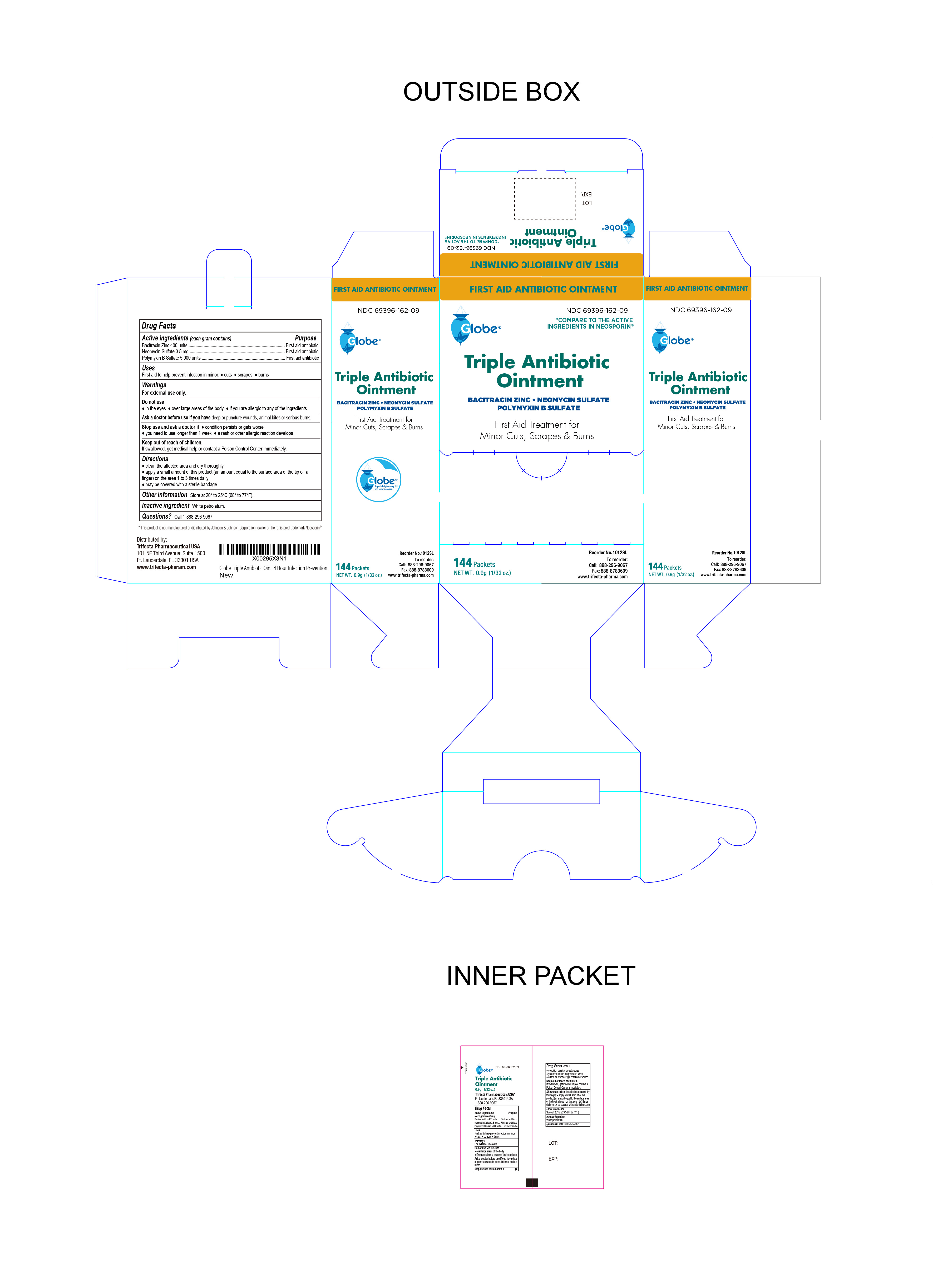 DRUG LABEL: Triple Antibiotic
NDC: 69396-162 | Form: OINTMENT
Manufacturer: TRIFECTA PHARMACEUTICALS USA LLC
Category: otc | Type: HUMAN OTC DRUG LABEL
Date: 20251014

ACTIVE INGREDIENTS: BACITRACIN ZINC 400 [USP'U]/1 g; NEOMYCIN SULFATE 3.5 mg/1 g; POLYMYXIN B SULFATE 5000 [USP'U]/1 g
INACTIVE INGREDIENTS: WHITE PETROLATUM

Triple Antibiotic Ointment

Active ingredients (each gram contains)

Bacitracin zinc 400 units
Neomycin sulfate 3.5 mg
Polymyxin B sulfate 5,000 units

Purpose

First aid antibiotic

Keep out of reach of children. If swallowed, get medical help or contact a Poison Control Center right away.

INDICATIONS AND USAGE

Uses first aid to help prevent infection in minor:● cuts ● scrapes ● burns

Warnings For external use only.

Do not use● in the eyes ● over large areas of the body

● if you are allergic to any of the ingredients.

Ask a doctor before use if you have

● deep or puncture wounds ● animal bites ● serious burns.

Stop use and ask a doctor if● condition persists or gets worse

● you need to use longer than 1 week

● a rash or other allergic reaction develops

Directions

● clean the affected area and dry thoroughly.

● apply a small amount of this product (an amount equal to the surface area of the tip of a finger) on the area 1 to 3 times daily

● may be covered with a sterile bandage.

Inactive ingredient White Petrolatum

Other information

● store at 20° to 25°C (68° to 77°F)

Questions? Call 1-888-296-9067

Distributed by:
Trifecta Pharmaceuticals USA™
101 NE Third Avenue, Suite 1500
Ft. Lauderdale, FL 33301, USA
1-888-296-9067

This product is not manufactured or distributed by Johnson & Johnson Corporation, owner of the registered trademark Neosporin®

reorder no. 1012SL